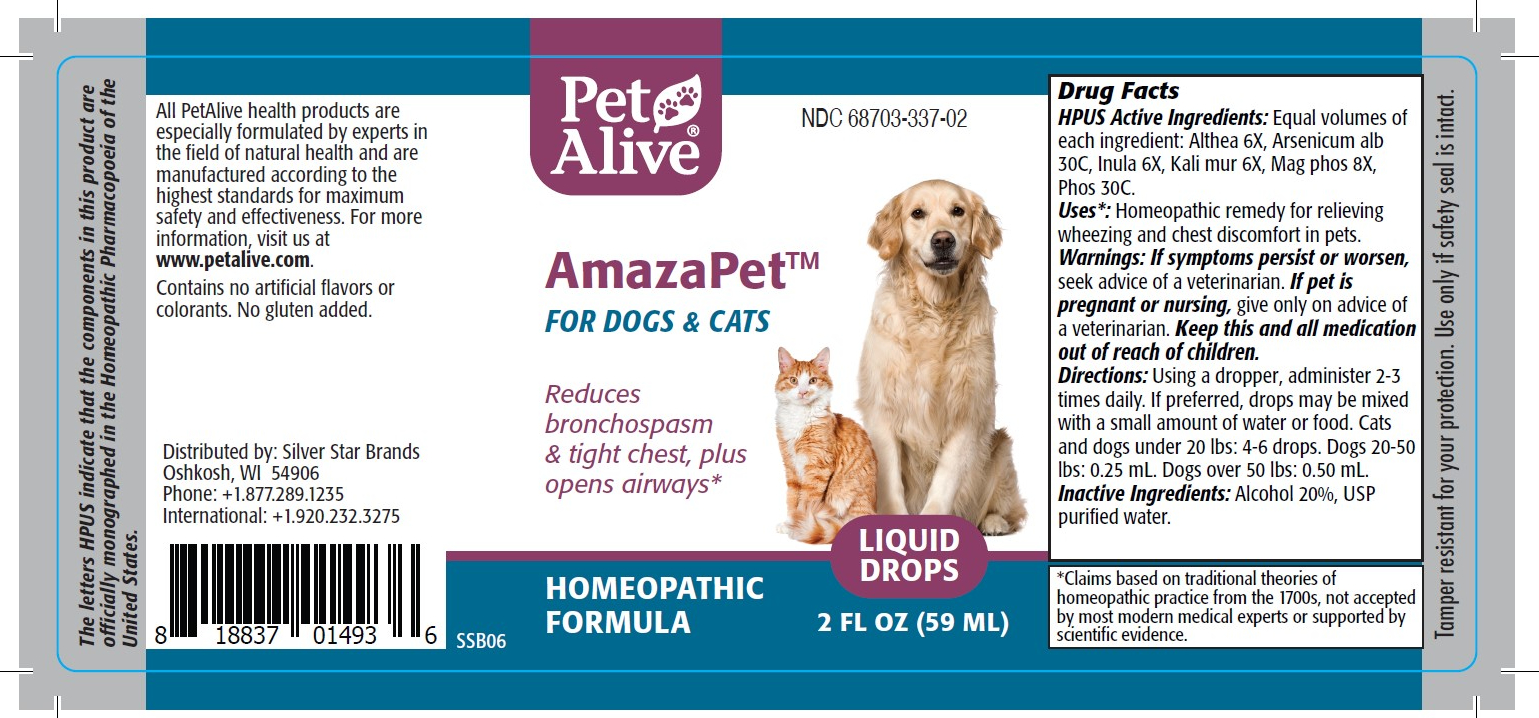 DRUG LABEL: PetAlive AmazaPet
NDC: 68703-337 | Form: LIQUID
Manufacturer: SILVER STAR BRANDS
Category: homeopathic | Type: OTC ANIMAL DRUG LABEL
Date: 20251216

ACTIVE INGREDIENTS: ALTHAEA OFFICINALIS ROOT 6 [hp_X]/59 mL; ARSENIC TRIOXIDE 30 [hp_C]/59 mL; INULA HELENIUM ROOT 6 [hp_X]/59 mL; POTASSIUM CHLORIDE 6 [hp_X]/59 mL; MAGNESIUM PHOSPHATE, DIBASIC TRIHYDRATE 8 [hp_X]/59 mL; PHOSPHORUS 30 [hp_C]/59 mL
INACTIVE INGREDIENTS: ALCOHOL; Water

PetAlive AmazaPet

PURPOSE

Reduces bronchospasm and tight chests, plus opens airways

HPUS Active Ingredients:

Althea 6X
Arsenicum alb 30C
Inula 6X
Kali mur 6X
Mag phos 8X
Phos 30C

INDICATIONS AND USAGE

Uses: Homeopathic remedy for relieving wheezing and chest discomfort.

WARNINGS

Warnings: If symptoms persist or worsen, seek advice of a veterinarian.

PREGNANCY OR BREAST FEEDING

If pet is pregnant or nursing, give only on advice of a veterinarian.

KEEP OUT OF REACH OF CHILDREN

Keep this and all medication out of reach of children.

DOSAGE AND ADMINISTRATION

Directions: Using a dropper, administer 2-3 times daily. If preferred, drops may be mixed with a small amount of water or food. Cats and dogs under 20 lbs: 4-6 drops. Dogs 20-50 Ibs: 0.25 mL. Dogs over 50 lbs: 0.50 mL.

Inactive Ingredients: Alcohol 20%, USP purified water.

INFORMATION FOR OWNERS/CAREGIVERS

The letters HPUS indicate that the components in this product are officially monographed in the Homeopathic Pharmacopoeia of the United States.

All PetAlive health products are especially formulated by experts in the field of natural health and are manufactured according to the highest standards for maximum safety and effectiveness. For more information, visit us at www.petalive.com.

Contains no artificial flavors or colorants. No gluten added.

Distributed by: Silver Star Brands
Oshkosh, WI 54906
Phone: +1.877.289.1235
International: +1.920.232.3275

STORAGE AND HANDLING

Tamper resistant seal for your protection. Use only if safety seal is intact.